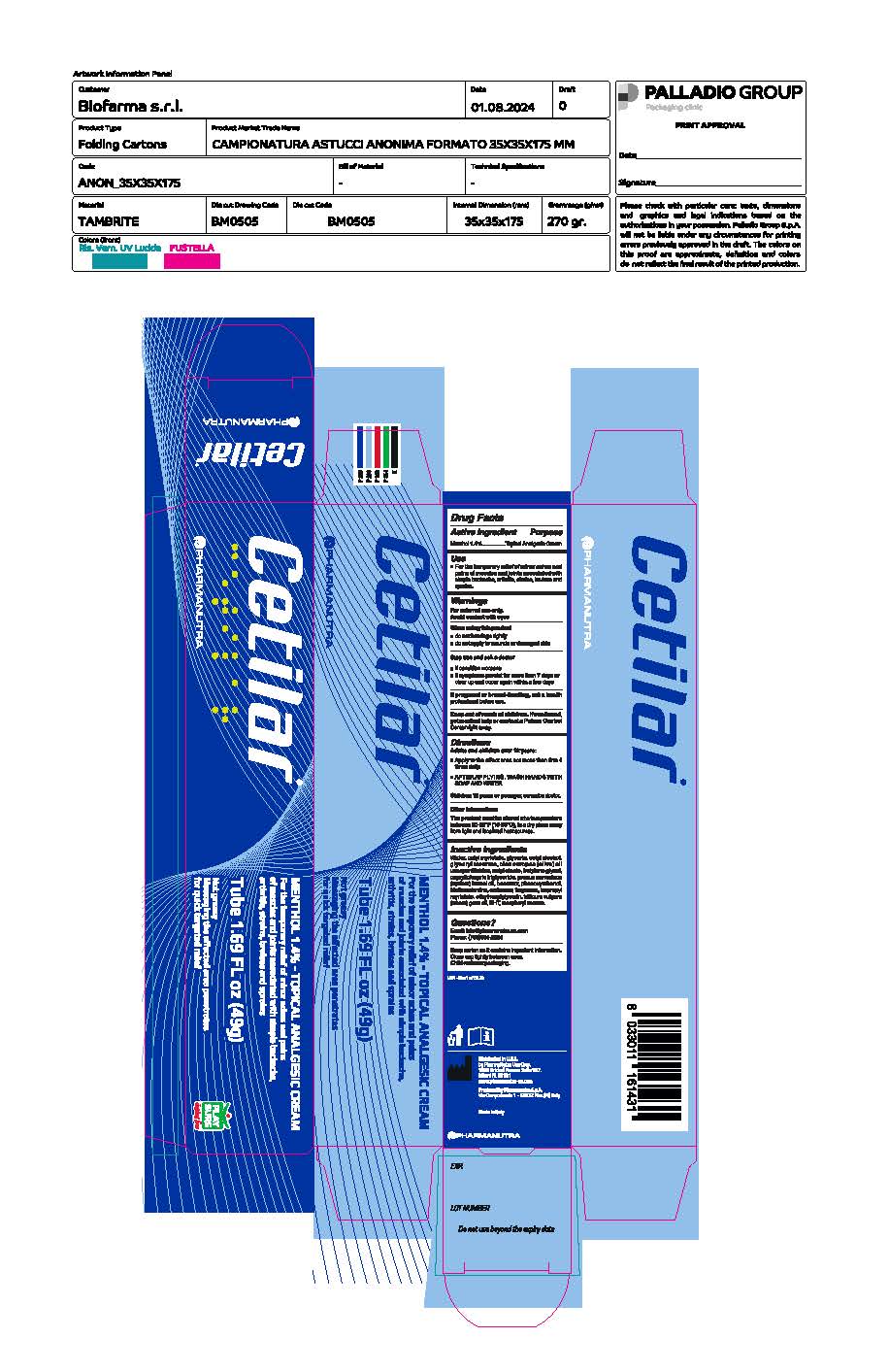 DRUG LABEL: Cetilar
NDC: 84797-000 | Form: CREAM
Manufacturer: PharmaNutra Usa Corp.
Category: otc | Type: HUMAN OTC DRUG LABEL
Date: 20250204

ACTIVE INGREDIENTS: MENTHOL 1.4 g/100 g
INACTIVE INGREDIENTS: GLYCERIN; BUTYLENE GLYCOL; APRICOT SEED OIL; WATER; GLYCERYL STEARATE; PHENOXYETHANOL; .ALPHA.-TOCOPHEROL ACETATE, D-; CAPRYLIC/CAPRIC TRIGLYCERIDE; TRIETHANOLAMINE; WHEAT GERM OIL UNSAPONIFIABLES; BEESWAX; POLYACRYLIC ACID (8000 MW); CETYL ALCOHOL; BUTYLATED HYDROXYTOLUENE; CETYL MYRISTATE; PERFLUOROPOLYMETHYLISOPROPYL ETHER; ISOPROPYL MYRISTATE; ETHYLHEXYLGLYCERIN

Cetilar

Active Ingredient

Menthol 1.4%

Purpose

Topical Analgesic

Use

For the temporary relief of minor aches and pains of muscles and joints associated with simple backache, arthritis, strains, bruises and sprains.

Warnings

For external use only. Avoid contact with eyes

When using this product

- Do not bandage tightly
- do not apply to wounds or damage skin

Stop use and ask a doctor

- if condition worsens
- if symptoms persist for more than 7 days or clear up and occur again within a few days

If pregnant or breast-feeding

ask a health professional before use

Keep out of reach of children

If swallowed, get medical help or contact a Poison Control Center right away

Directions

Adults and children over 12 years:

- Apply to the affect area not more than 3 to 4 times daily
- After applying, wash hands with soap and water

Children 12 years or younger, consult a doctor

Other Information

The product must be stored at temperature between 50-86 °F (10-30ºC), in a dry place away from light localized heat sources.

Inactive ingredients

water, cetyl myristate, Glycerin, Cetyl alcohol, Glyceryl stearate, olea europea (olive) oil unsaponifiables, cetyloleate, Butylene glycol, Caprylic capric triglyceride, prunus armeniaca (apricot) kenel oil, Beeswax, Phenoxyethanol, Triethanolamine, carbomer, fragrance, isopropyl myristate, ethylhexylglycerin, triticum vulgare (wheat) germ oil, BHT, tocopheryl acetate.